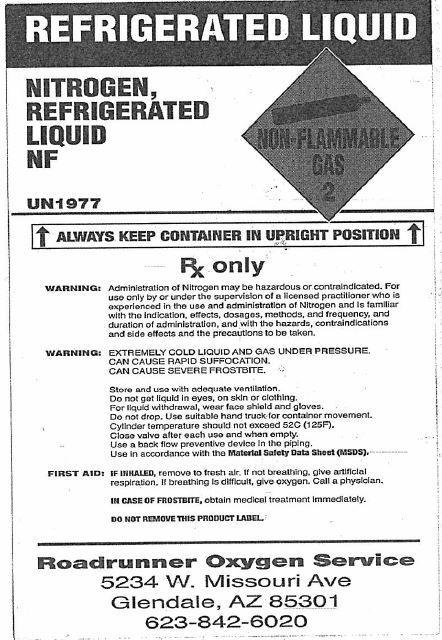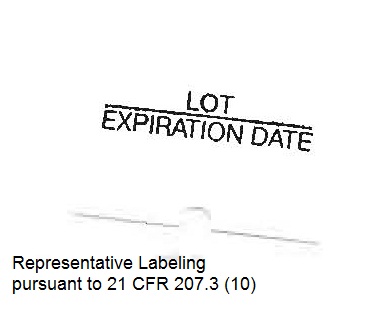 DRUG LABEL: Nitrogen
NDC: 67795-100 | Form: GAS
Manufacturer: Roadrunner Oxygen Service, Inc.
Category: prescription | Type: HUMAN PRESCRIPTION DRUG LABEL
Date: 20251202

ACTIVE INGREDIENTS: NITROGEN 99 L/100 L

Nitrogen

Principal for Nitrogen Product

REPRESENTATIVE LABELING ONLY

NITROGEN, REFRIGERATED LIQUID

NF

NON-FLAMMABLE 2

UN1977

ALWAYS KEEP CONTAINER IN UPRIGHT POSITION

WARNING: EXTREMELY COLD LIQUID AND GAS UNDER PRESSURE.
CAN CAUSE RAPID SUFFOCATION.
CAN CAUSE SEVERE FROSTBITE.
Store and use with adequate ventilation.
Do not get liquid in eyes, on skin, or clothing.
For liquid withdrawal, wear face shield and gloves.
Do not drop. Use hand truck for container movement.
Close valve after each use and when empty.
Use in accordance with the Material Safety Data Sheet (MSDS).

FIRST AID: IF INHALED, remove to fresh air. If not breathing,
give artificial respiration. If breathing is difficult, give
oxygen. Call a physician.
IN CASE OF FROSTBITE, obtain medical treatment
immediately.

CAUTION: Rx Only.

WARNING: Administration of Nitrogen may be hazardous or
contraindicated. For use only by or under the super-
vision of a licensed practitioner who is experienced in
the use and administration of Nitrogen and is familiar
with the indications, effects, dosages, methods, and
frequency and duration of administration, and with the
hazards, contraindications and side effects and the
precautions to be taken.
DO NOT REMOVE THIS PRODUCT LABEL